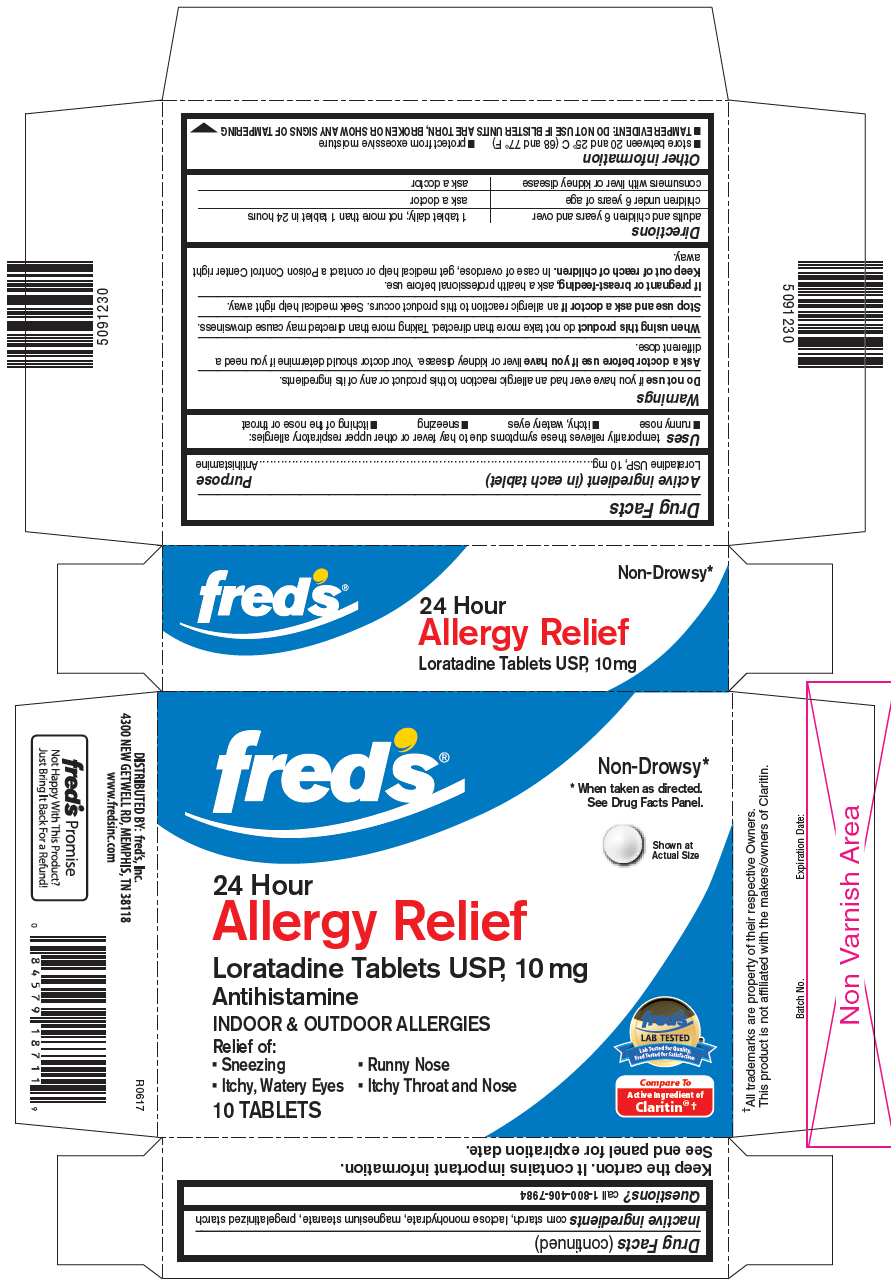 DRUG LABEL: Loratadine
NDC: 55315-528 | Form: TABLET
Manufacturer: Fred's Inc.
Category: otc | Type: HUMAN OTC DRUG LABEL
Date: 20191213

ACTIVE INGREDIENTS: LORATADINE 10 mg/1 1
INACTIVE INGREDIENTS: STARCH, CORN; LACTOSE MONOHYDRATE; MAGNESIUM STEARATE

Drug Facts

ACTIVE INGREDIENT (IN EACH TABLET)

Loratadine USP, 10 mg

PURPOSE

Antihistamine

USES

Temporarily relieves these symptoms due to hay fever or other upper respiratory allergies:

- runny nose
- itchy, watery eyes
- sneezing
- itching of the nose or throat

WARNINGS

Do not use

If you have ever had an allergic reaction to this product or any of its ingredients.

Ask a doctor before use if you have

Liver or kidney disease. Your doctor should determine if you need a different dose.

When using this product

Do not take more than directed. Taking more than directed may cause drowsiness.

Stop use and ask a doctor if

An allergic reaction to this product occurs. Seek medical help right away.

If pregnant or breast-feeding

Ask a health professional before use.

Keep out of reach of children.

In case of overdose, get medical help or contact a Poison Control Center right away.

DIRECTIONS

adults and children 6 years and over | 1 tablet daily; not more than 1 tablet in 24 hours
children under 6 years of age | ask a doctor
consumers with liver or kidney disease | ask a doctor

OTHER INFORMATION

- store between 20 and 25° C (68 and 77° F)
- protect from excessive moisture
- TAMPER EVIDENT: DO NOT USE IF BLISTER UNITS ARE TORN, BROKEN OR SHOW ANY SIGNS OF TAMPERING.

INACTIVE INGREDIENTS

Corn starch, lactose monohydrate, magnesium stearate, pregelatinized starch

QUESTIONS?

Call 1-800-406-7984

PRINCIPAL DISPLAY PANEL

fred's®

Non-Drowsy*

* When taken as directed.

See Drug Facts Panel.

24 Hour

Allergy Relief

Loratadine Tablets USP, 10 mg

Antihistamine

INDOOR & OUTDOOR ALLERGIES

Relief of:

- Sneezing
- Runny Nose
- Itchy, Watery Eyes
- Itchy Throat and Nose

10 TABLETS

Compare to Active Ingredient of Claritin®†